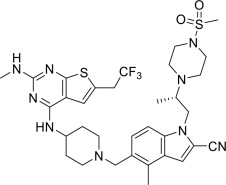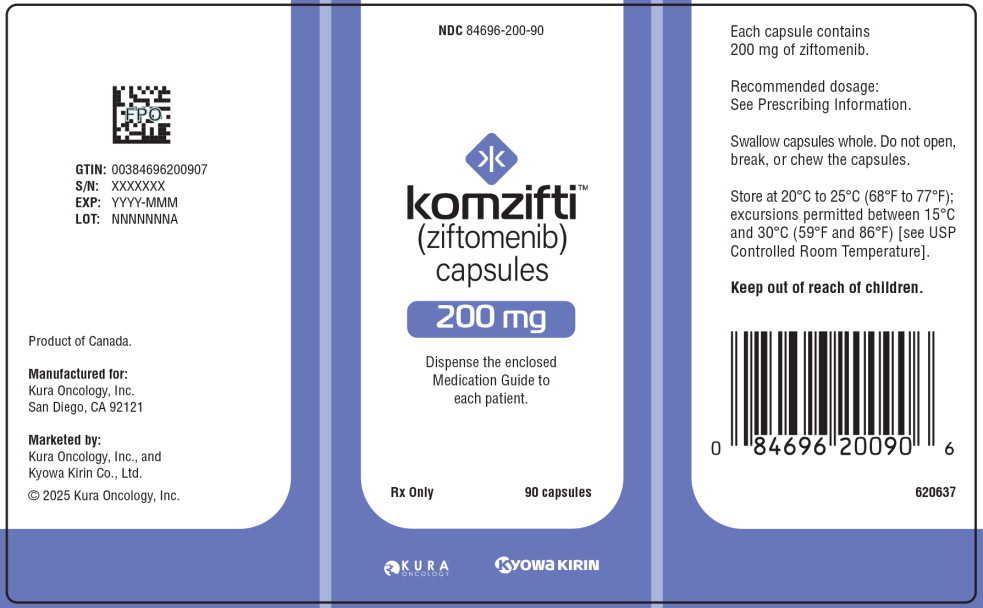 DRUG LABEL: Komzifti
NDC: 84696-200 | Form: CAPSULE
Manufacturer: Kura Oncology, Inc.
Category: prescription | Type: HUMAN PRESCRIPTION DRUG LABEL
Date: 20251209

ACTIVE INGREDIENTS: ziftomenib 200 mg/1 1
INACTIVE INGREDIENTS: Microcrystalline cellulose; Mannitol; Sodium lauryl sulfate; Croscarmellose sodium; Magnesium stearate

HIGHLIGHTS OF PRESCRIBING INFORMATION

These highlights do not include all the information needed to use KOMZIFTI safely and effectively. See full prescribing information for KOMZIFTI.
KOMZIFTITM (ziftomenib) capsules, for oral use
Initial U.S. Approval: 2025

WARNING: DIFFERENTIATION SYNDROME

See full prescribing information for complete boxed warning.

Differentiation syndrome, which can be fatal, has occurred with KOMZIFTI. If differentiation syndrome is suspected, interrupt KOMZIFTI and initiate oral or intravenous corticosteroids with hemodynamic and laboratory monitoring until symptom resolution; resume KOMZIFTI upon symptom improvement. (2.5, 5.1, 6.1)

1 INDICATIONS AND USAGE

KOMZIFTI is a menin inhibitor indicated for the treatment of adult patients with relapsed or refractory acute myeloid leukemia (AML) with a susceptible nucleophosmin 1 (NPM1) mutation who have no satisfactory alternative treatment options. (1)

2 DOSAGE AND ADMINISTRATION

- Select patients for treatment with KOMZIFTI based on the presence of an NPM1 mutation. (2.1)
- Recommended dosage: 600 mg orally once daily until disease progression or unacceptable toxicity. For patients without confirmed disease progression or unacceptable toxicity, treat for a minimum of 6 months to allow time for a clinical response. (2.2)
- See Full Prescribing Information for administration instructions and dosage modifications. (2.3, 2.4, 2.5)

3 DOSAGE FORMS AND STRENGTHS

Capsules: 200 mg (3)

4 CONTRAINDICATIONS

None. (4)

5 WARNINGS AND PRECAUTIONS

QTc Interval Prolongation: Monitor electrocardiograms and electrolytes. Correct hypokalemia and hypomagnesemia prior to treatment. Interrupt KOMZIFTI if the QTc interval is > 500 ms. (5.2)

Embryo-Fetal Toxicity: Can cause fetal harm. Advise patients of reproductive potential of the potential risk to a fetus and to use effective contraception. (5.3, 8.1, 8.3)

6 ADVERSE REACTIONS

The most common adverse reactions (≥20%) are infection without an identified pathogen, hemorrhage, diarrhea, nausea, fatigue, edema, bacterial infection, musculoskeletal pain, differentiation syndrome, pruritus, febrile neutropenia, and transaminases increased. (6.1)

The most common laboratory abnormalities (≥10%) are aspartate aminotransferase increased, potassium decreased, albumin decreased, alanine aminotransferase increased, sodium decreased, creatinine increased, alkaline phosphatase increased, bilirubin increased, potassium increased. (6.1)

To report SUSPECTED ADVERSE REACTIONS, contact Kura Oncology, Inc., at 1-844-KURAONC, or FDA at 1-800-FDA-1088 or www.fda.gov/medwatch.

7 DRUG INTERACTIONS

Strong or Moderate CYP3A4 Inhibitors: Monitor more frequently for adverse reactions. (7.1)

Strong or Moderate CYP3A4 Inducers: Avoid concomitant use. (7.1)

Proton Pump Inhibitors: Avoid concomitant use. (2.4, 7.1)

H2 Receptor Antagonists and Antacids: Avoid concomitant use. If concomitant use cannot be avoided, modify KOMZIFTI administration time. (2.4, 7.1)

Drugs that Prolong the QTc Interval: Avoid concomitant use. If concomitant use is unavoidable, monitor patients more frequently for QTc interval prolongations. (5.2, 7.1)

8 USE IN SPECIFIC POPULATIONS

Lactation: Advise not to breastfeed. (8.2)

FULL PRESCRIBING INFORMATION

WARNING: DIFFERENTIATION SYNDROME

Differentiation syndrome, which can be fatal, has occurred with KOMZIFTI. Signs and symptoms may include fever, joint pain, hypotension, hypoxia, dyspnea, rapid weight gain or peripheral edema, pleural or pericardial effusions, pulmonary infiltrates, acute kidney injury, and rashes. If differentiation syndrome is suspected, interrupt KOMZIFTI and initiate oral or intravenous corticosteroids with hemodynamic and laboratory monitoring until symptom resolution; resume KOMZIFTI upon symptom improvement [see Dosage and Administration (2.5), Warnings and Precautions (5.1), and Adverse Reactions (6.1)].

1 INDICATIONS AND USAGE

KOMZIFTI is indicated for the treatment of adult patients with relapsed or refractory acute myeloid leukemia (AML) with a susceptible nucleophosmin 1 (NPM1) mutation who have no satisfactory alternative treatment options [see Dosage and Administration (2.1), Clinical Pharmacology (12.1), and Clinical Studies (14)].

2 DOSAGE AND ADMINISTRATION

2.1 Patient Selection

Select patients for the treatment of relapsed or refractory AML with KOMZIFTI based on the presence of an NPM1 mutation [see Clinical Studies (14)].

An FDA-approved test for the detection of NPM1 mutations is not currently available.

2.2 Recommended Dosage

The recommended dosage of KOMZIFTI is 600 mg taken orally once daily until disease progression or unacceptable toxicity. Do not start KOMZIFTI until the white blood cell (WBC) count is reduced to less than 25 x 10⁹/L. For patients without confirmed disease progression or unacceptable toxicity, treatment for a minimum of 6 months is recommended to allow time for a clinical response.

2.3 Administration Instructions

- Administer KOMZIFTI once daily on an empty stomach (at least 1 hour before or 2 hours after a meal) [see Clinical Pharmacology (12.3)].
- Administer KOMZIFTI orally at about the same time each day.
- Swallow capsules whole. Do not open, break, or chew the capsules.
- If a dose of KOMZIFTI is missed or not taken at the usual time, administer the dose as soon as possible on the same day and at least 12 hours prior to the next scheduled dose. Return to the normal schedule the following day. Do not administer 2 doses within 12 hours.

2.4 Dosage Modifications for Concomitant Use of Acid-Reducing Agents

Avoid concomitant use of proton pump inhibitors (PPIs) with KOMZIFTI.

Avoid concomitant use of a histamine-2 (H2) receptor antagonist or a locally acting antacid with KOMZIFTI [see Drug Interactions (7.1)]. If concomitant use cannot be avoided:

- Take KOMZIFTI 2 hours before or 10 hours after administration of an H2 receptor antagonist.
- Take KOMZIFTI 2 hours before or 2 hours after administration of a locally acting antacid.

2.5 Dosage Modifications for Adverse Reactions

Manage any abnormalities promptly [see Warnings and Precautions (5.1, 5.2) and Adverse Reactions (6.1)].

Interrupt or reduce dose for adverse reactions as per Table 1 and Table 2.

Table 1 Recommended Management and Dosage Modifications for KOMZIFTI for Adverse Reactions
Adverse Reactiona | Recommended Action
Differentiation syndrome [see Warnings and Precautions (5.1)] | - If differentiation syndrome is suspected, interrupt KOMZIFTI. - Administer systemic corticosteroids and initiate hemodynamic monitoring until symptom resolution and for a minimum of 3 days and provide supportive care. - Resume KOMZIFTI at the same dose level when signs and symptoms improve and are Grade ≤ 2b.
Noninfectious leukocytosis (e.g., sudden or significant white blood cell (WBC) increase, including WBC doubling within the first 2 weeks of administration or an absolute increase of 10 x 10^9/L) | - Evaluate for differentiation syndrome. - Initiate treatment with hydroxyurea, as per standard institutional practices, and leukapheresis if clinically indicated. - Taper hydroxyurea only after leukocytosis improves or resolves. - Interrupt KOMZIFTI if leukocytosis is not controlled with hydroxyurea within 48 hours. If interrupted, resume KOMZIFTI at the same dose level once WBC counts are controlled.
Nonhematological adverse reactions Grade ≥ 3b [see Adverse Reactions (6.1)] | - Interrupt KOMZIFTI until recovery to Grade ≤ 2b. - Resume KOMZIFTI at the same dose level. - If the same Grade ≥ 3 toxicity recurs, interrupt KOMZIFTI until recovery to Grade ≤ 2b. - Restart KOMZIFTI at a reduced dosec.
a Cancer Institute Common Terminology Criteria for Adverse Events (NCI CTCAE) version 5.0.
b Grade 1 is mild, Grade 2 is moderate, Grade 3 is severe, Grade 4 is life-threatening.
c See Table 2 for the reduced dose levels.

Table 2 Recommended Dosage Reductions for KOMZIFTI for Adverse Reactions
 | Recommended Dosage
First dose reduction | 400 mg orally once daily
Second dose reduction | 200 mg orally once daily
*Permanently discontinue KOMZIFTI in patients unable to tolerate 200 mg orally once daily following second dose reduction.

3 DOSAGE FORMS AND STRENGTHS

Capsules of ziftomenib are available in 200 mg strength. The capsules are white and are imprinted with “ZIF 200” in black ink.

4 CONTRAINDICATIONS

None.

5 WARNINGS AND PRECAUTIONS

5.1 Differentiation Syndrome

KOMZIFTI can cause fatal or life-threatening differentiation syndrome. Differentiation syndrome is associated with rapid proliferation and differentiation of myeloid cells. Symptoms of differentiation syndrome, including those seen in patients treated with KOMZIFTI, may include fever, hypoxia, joint pain, hypotension, dyspnea, rapid weight gain or peripheral edema, pleural or pericardial effusions, acute kidney injury, and rashes.

In the clinical trial, differentiation syndrome occurred in 29 (26%) of 112 patients with relapsed or refractory AML with an NPM1 mutation who were treated with KOMZIFTI at the recommended dosage. Differentiation syndrome was Grade 3 in 13% and fatal in two patients. In broader evaluation of all patients with any genetic form of AML treated with KOMZIFTI monotherapy in clinical trials, differentiation syndrome occurred in 25% of patients. Four fatal cases of differentiation syndrome occurred out of 39 patients with KMT2A-rearranged AML treated with KOMZIFTI. KOMZIFTI is not approved for use in patients with KMT2A-rearranged AML.

In the 112 patients with an NPM1 mutation, differentiation syndrome was observed with and without concomitant hyperleukocytosis, in as early as 3 days and up to 46 days after KOMZIFTI initiation. The median time to onset was 15 days. Two patients experienced more than one differentiation syndrome event. Treatment was interrupted and resumed in 15 (13%) patients, while it was permanently discontinued in 2 (2%) patients [see Adverse Reactions (6.1)].

Prior to starting treatment with KOMZIFTI, reduce the WBC counts to less than 25 x 10⁹/L. If differentiation syndrome is suspected, interrupt KOMZIFTI, initiate oral or intravenous corticosteroids (e.g., dexamethasone 10 mg every 12 hours) for a minimum of 3 days with hemodynamic and laboratory monitoring. Resume treatment with KOMZIFTI at the same dose level when signs and symptoms improve and are Grade 2 or lower. Taper corticosteroids over a minimum of 3 days after adequate control or resolution of symptoms [see Dosage and Administration (2.5)]. Symptoms of differentiation syndrome may recur with premature discontinuation of corticosteroid treatment.

5.2 QTc Interval Prolongation

KOMZIFTI can cause QT (QTc) interval prolongation [see Clinical Pharmacology (12.2)]. In the clinical trial, QTc interval prolongation was reported as an adverse reaction in 12% of 112 patients treated with KOMZIFTI at the recommended dosage for relapsed or refractory AML with an NPM1 mutation. QTc interval prolongation was Grade 3 in 8% of patients. The heart-rate corrected QT interval (using Fridericia's method) (QTcF) was greater than 500 msec in 9% of patients, and the increase from baseline QTcF was greater than 60 msec in 12% of patients. KOMZIFTI dose reduction was required for 1% of patients due to QTc interval prolongation [see Adverse Reactions (6.1)]. QTc prolongation occurred in 14% of the 42 patients less than 65 years of age and in 10% of the 70 patients 65 years of age or older.

Correct electrolyte abnormalities, including hypokalemia and hypomagnesemia, prior to treatment with KOMZIFTI. Perform an ECG prior to initiation of treatment with KOMZIFTI, and do not initiate KOMZIFTI in patients with QTcF > 480 msec. Perform an ECG at least once weekly for the first four weeks on treatment, and at least monthly thereafter. Interrupt KOMZIFTI if the QTc interval is > 500 ms or the change from baseline is > 60 ms (Grade 3) [see Dosage and Administration (2.5)]. In patients with congenital long QTc syndrome, congestive heart failure, electrolyte abnormalities, or those who are taking medications known to prolong the QTc interval, more frequent ECG monitoring may be necessary. Concomitant use of KOMZIFTI with drugs known to prolong the QTc interval may increase the risk of QTc interval prolongation [see Drug Interactions (7.1), Clinical Pharmacology (12.2)].

5.3 Embryo-Fetal Toxicity

Based on findings in animals and its mechanism of action, KOMZIFTI can cause embryo-fetal harm when administered to a pregnant woman. In animal reproduction studies, oral administration of ziftomenib to pregnant mice during the period of organogenesis caused adverse developmental outcomes, including embryo-fetal mortality, structural abnormalities, and altered fetal growth at approximately 0.3 times the steady-state clinical exposure based on the area under the concentration-time curve (AUC) at the recommended human dose.

Advise pregnant women of the potential risk to the fetus. Advise females of reproductive potential to use effective contraception during treatment with KOMZIFTI and for 6 months after the last dose. Advise males with female partners of reproductive potential to use effective contraception during treatment with KOMZIFTI and for 3 months after the last dose [see Use in Specific Populations (8.1, 8.3)].

6 ADVERSE REACTIONS

The following clinically significant adverse reactions are described elsewhere in the labeling:

- Differentiation Syndrome [see Warnings and Precautions (5.1)]
- QTc Interval Prolongation [see Warnings and Precautions (5.2)]

6.1 Clinical Trials Experience

Because clinical trials are conducted under widely varying conditions, adverse reaction rates observed in the clinical trials of a drug cannot be directly compared to rates in the clinical trials of another drug and may not reflect the rates observed in practice.

Relapsed or Refractory AML with an NPM1 Mutation

The safety of KOMZIFTI for the treatment of patients with relapsed or refractory AML with an NPM1 mutation was evaluated in KO-MEN-001 [see Clinical Studies (14)]. Patients received KOMZIFTI 600 mg once daily (n=112). The median duration of exposure to KOMZIFTI was 2.2 months (range 0.1 to 21.5 months).

Fatal adverse reactions occurred in 4 (4%) patients who received KOMZIFTI, including 2 with differentiation syndrome, 1 with infection, and 1 with sudden death. Serious adverse reactions were reported in 79% of patients who received KOMZIFTI. Serious adverse reactions occurring in ≥ 5% of patients included infection without an identified pathogen (29%), febrile neutropenia (18%), bacterial infection (16%), differentiation syndrome (16%), and dyspnea (6%).

Dosage interruption of KOMZIFTI due to an adverse reaction occurred in 54% of patients. Adverse reactions that required dose interruption in ≥ 2% of patients included infection without an identified pathogen (15%), differentiation syndrome (13%), febrile neutropenia (5%), pyrexia (4%), electrocardiogram QT prolonged (4%), leukocytosis (4%), bacterial infection (3%), cardiac failure (2%), cholecystitis (2%), diarrhea (2%), pruritus (2%), and thrombosis (2%). Dose reduction of KOMZIFTI due to an adverse reaction occurred in 4% of patients. Permanent discontinuation of KOMZIFTI due to an adverse reaction occurred in 21% of patients. Adverse reactions that required permanent discontinuation of KOMZIFTI in ≥ 2% of patients were infection without an identified pathogen (8%), bacterial infection (4%), cardiac arrest (2%), and differentiation syndrome (2%).

The most common (≥ 20%) adverse reactions, including laboratory abnormalities, were aspartate aminotransferase increased, infection without an identified pathogen, potassium decreased, albumin decreased, alanine aminotransferase increased, sodium decreased, creatinine increased, alkaline phosphatase increased, hemorrhage, diarrhea, nausea, fatigue, edema, bacterial infection, musculoskeletal pain, bilirubin increased, potassium increased, differentiation syndrome, pruritus, febrile neutropenia, and transaminases increased.

Table 3 summarizes the adverse reactions in KO-MEN-001.

Table 3 Adverse Reactions Reported in ≥20% (Any Grade) or ≥5% (Grade 3 or 4) of Patients with Relapsed or Refractory AML
Adverse Reaction | KOMZIFTI N=112
Adverse Reaction | All Grades† (%) | Grade 3 or 4 (%)
Infections and infestations
Infection without identified pathogena | 52 | 38
Bacterial infectionb | 28 | 17
Viral infectionc | 16 | 5
Vascular disorders
Hemorrhaged | 38 | 8
Hypertension | 11 | 5
Gastrointestinal disorders
Diarrheae* | 36 | 5
Nauseaf* | 35 | 2
General disorders and administration site conditions
Fatigueg | 34 | 8
Edemah* | 30 | 3
Musculoskeletal and connective tissue disorders
Musculoskeletal paini | 28 | 4
Neoplasms benign, malignant, and unspecified (incl cysts and polyps)
Differentiation syndrome | 26 | 13
Skin and subcutaneous
Pruritusj* | 23 | 0
Blood and lymphatic system disorder
Febrile neutropenia | 22 | 22
Leukocytosisk* | 16 | 5
Investigations
Transaminases increasedl | 21 | 8
Electrocardiogram QT prolonged* | 12 | 8
Renal and urinary disorders
Renal impairmentm | 19 | 6
Respiratory, thoracic, and mediastinal disorders
Hypoxia | 9 | 5
†Includes the following fatal adverse reactions: infection (n=1) and differentiation syndrome (n=2).
*No Grade 4 events were reported for this adverse reaction.
a Includes abdominal abscess, abscess limb, anal abscess, anorectal infection, bronchitis, conjunctivitis, device related infection, device related sepsis, diverticulitis, emphysematous cystitis, enterocolitis infectious, gingivitis, hordeolum, infection, large intestine infection, nail infection, necrotizing fasciitis, penile infection, periodontitis, perirectal abscess, peritonitis, pneumonia, postoperative abscess, respiratory tract infection, rhinitis, sepsis, septic shock, sinusitis, skin infection, soft tissue infection, tooth infection, upper respiratory tract infection, urosepsis, vaginal infection, vascular device infection, wound infection.
b Includes bacteremia, bacterial infection, bacterial pyelonephritis, breast cellulitis, cellulitis, clostridial infection, clostridium difficile colitis, clostridium difficile infection, enterobacter sepsis, enterococcal bacteremia, erysipelas, escherichia bacteremia, escherichia infection, escherichia sepsis, escherichia urinary tract infection, klebsiella bacteremia, klebsiella infection, klebsiella urinary tract infection, paronychia, pneumonia bacterial, pneumonia klebsiella, pseudomonal bacteremia, staphylococcal bacteremia.
c Includes adenovirus infection, COVID-19, genital herpes, herpes simplex reactivation, herpes virus infection, herpes zoster, nasal herpes, oral herpes, pneumonia influenzas, pneumonia parainfluenza viral, respiratory syncytial virus infection, rhinovirus infection.
d Includes angina bullosa hemorrhagic, bladder tamponade, catheter site hematoma, conjunctival hemorrhage, contusion, disseminated intravascular coagulation, ecchymosis, epistaxis, gastric hemorrhage, gastrointestinal hemorrhage, gingival bleeding, hematemesis, hematochezia, hematoma, hematuria, hemoptysis, hemorrhage, hemorrhoidal hemorrhage, hyperfibrinolysis, injection site hematoma, injection site hemorrhage, lower gastrointestinal hemorrhage, melaena, mouth hemorrhage, oral blood blister, petechiae, purpura, rectal hemorrhage, retinal hemorrhage, shock hemorrhagic, skin hemorrhage, subdural hematoma, tongue hemorrhage, traumatic hematoma, upper gastrointestinal hemorrhage, vaginal hemorrhage, vitreous hemorrhage.
e Includes diarrhea, colitis, colitis erosive.
f Includes nausea, vomiting.
g Includes fatigue, asthenia, malaise.
h Includes edema, edema peripheral, generalized edema, localized edema, peripheral swelling.
i Includes arthralgia, back pain, bone pain, flank pain, musculoskeletal chest pain, musculoskeletal pain, myalgia, neck pain, pain in extremity.
j Includes pruritus, nasal pruritus.
k Includes white blood cell count increased, leukocytosis, hyperleukocytosis.
l Includes transaminases increased, alanine aminotransferase increased, aspartate aminotransferase increased, gamma-glutamyl transferase increased, hypertransaminasemia.
m Includes renal impairment: acute kidney injury, azotemia, blood creatinine increased, blood urea increased, chronic kidney disease, postrenal failure, renal failure.

Table 4 summarizes the laboratory abnormalities in KO-MEN-001.

Table 4 Selected New or Worsening Laboratory Abnormalities in Patients with Relapsed or Refractory AML
Laboratory Abnormality | KOMZIFTI
Laboratory Abnormality | Grades 1-4* (%) | Grade 3-4* (%)
Aspartate aminotransferase increased | 53 | 4
Potassium decreased | 52 | 22
Albumin decreased | 51 | 5
Alanine aminotransferase increased | 50 | 6
Sodium decreased | 49 | 3
Creatinine increased | 45 | 4
Alkaline phosphatase increased | 41 | 5
Bilirubin increased | 27 | 6
Potassium increased | 26 | 6
*The denominator used to calculate the rate varied from 108 to 110 based on the number of patients with a baseline value and at least one post-baseline value.

7 DRUG INTERACTIONS

7.1 Effect of Other Drugs on KOMZIFTI

Strong or Moderate CYP3A4 Inhibitors

Monitor patients more frequently for KOMZIFTI-associated adverse reactions.

Ziftomenib is primarily metabolized by CYP3A. Concomitant use of KOMZIFTI with strong or moderate CYP3A4 inhibitors increases ziftomenib exposure [see Clinical Pharmacology (12.3)], which may increase the risk of adverse reactions such as QT prolongation.

Strong or Moderate CYP3A4 Inducers

Avoid concomitant use of KOMZIFTI with strong or moderate CYP3A4 inducers.

Ziftomenib is primarily metabolized by CYP3A. Concomitant use of KOMZIFTI with strong or moderate CYP3A4 inducers may decrease ziftomenib exposure [see Clinical Pharmacology (12.3)], which may reduce the efficacy of KOMZIFTI.

Gastric Acid Reducing Agents

Concomitant administration of ziftomenib with proton pump inhibitors (PPIs) decreases ziftomenib exposure [see Clinical Pharmacology (12.3)], which may reduce the efficacy of KOMZIFTI.

Avoid concomitant use of KOMZIFTI with PPIs.

Avoid concomitant use of KOMZIFTI with H2 receptor antagonists (H2RAs) or locally acting antacids. If concomitant use cannot be avoided, modify KOMZIFTI administration time [see Dosage and Administration (2.4)].

Drugs that Prolong the QT Interval

Avoid concomitant use of KOMZIFTI with other product(s) with a known potential to prolong the QTc interval. If concomitant use cannot be avoided, obtain ECGs when initiating, during concomitant use, and as clinically indicated [see Warnings and Precautions (5.2)]. Interrupt KOMZIFTI if the QTc interval is > 500 ms or the change from baseline is > 60 ms [see Dosage and Administration (2.5)].

Ziftomenib causes QTc interval prolongation [see Clinical Pharmacology (12.2)]. Concomitant use of KOMZIFTI with other products that prolong the QTc interval may result in a greater increase in the QTc interval and adverse reactions associated with QTc interval prolongation, including Torsades de pointes, other serious arrhythmias, and sudden death [see Warnings and Precautions (5.2)].

8 USE IN SPECIFIC POPULATIONS

8.1 Pregnancy

Risk Summary

Based on findings in animals and its mechanism of action [see Clinical Pharmacology (12.1)], KOMZIFTI can cause embryo-fetal harm when administered to a pregnant woman. There are no available data on KOMZIFTI use in pregnant women to evaluate for a drug-associated risk.

In animal reproduction studies, oral administration of ziftomenib to pregnant mice during the period of organogenesis resulted in adverse developmental outcomes, including embryo-fetal mortality, structural abnormalities, and altered fetal growth at maternal exposures approximately 0.3 times the human exposure (AUC) at the recommended dose (see Data). Advise pregnant women of the potential risk to a fetus.

In the U.S. general population, the estimated background risk of major birth defects and miscarriage in clinically recognized pregnancies is 2% to 4% and 15% to 20%, respectively.

Data

Animal Data

Ziftomenib was administered orally twice daily to pregnant mice at doses of 6, 20, and 60 mg/kg/day during organogenesis (gestation days 6-15). Decreased fetal body weight, embryo-fetal lethality, fetal external and skeletal malformations and variations (cleft palate, fused cervical arches, absent lumbar vertebrae fused and/or misaligned costal cartilage, absent or short rib, supernumerary site in the suture bone or split palatine of the skull, and/or fused, unossified, and/or incompletely ossified sternebrae) were noted at all doses. At the dose of 6 mg/kg/day in mice, the maternal exposure was approximately 0.3 times the human exposure at the recommended dose of 600 mg once daily.

8.2 Lactation

Risk Summary

There are no data on the presence of ziftomenib or its metabolites in human milk or the effects of ziftomenib or its metabolites on the breastfed child or milk production. Because of the potential for adverse reactions in the breastfed child, advise women not to breastfeed during treatment with KOMZIFTI and for 2 weeks after the last dose.

8.3 Females and Males of Reproductive Potential

Based on findings in animals and its mechanism of action, KOMZIFTI can cause fetal harm when administered to a pregnant woman [see Use in Specific Populations (8.1)].

Pregnancy Testing

Verify pregnancy status in females of reproductive potential prior to initiating KOMZIFTI.

Contraception

Females

Advise females of reproductive potential to use effective contraception during treatment with KOMZIFTI and for 6 months after the last dose.

Males

Advise males with female partners of reproductive potential to use effective contraception during treatment with KOMZIFTI and for 3 months after the last dose.

Infertility

Based on findings in animals, KOMZIFTI may impair fertility in females and males of reproductive potential. Findings in animals were not reversible after a 4-week recovery period [see Nonclinical Toxicology (13.1)].

8.4 Pediatric Use

Safety and effectiveness of KOMZIFTI in pediatric patients have not been established.

8.5 Geriatric Use

Of the 112 patients with relapsed or refractory AML with an NPM1 mutation treated with KOMZIFTI, 70 (63%) patients were 65 years of age or older and 31 (28%) were 75 years or older.

No overall differences in effectiveness, safety, or pharmacokinetics of KOMZIFTI were observed between patients aged 65 years or older and younger patients [see Clinical Studies (14) and Clinical Pharmacology (12.3)].

8.6 Renal Impairment

No dose adjustment is required for patients with mild or moderate (CLCr 30 to 89 mL/min) renal impairment. The effects of severe (CLCr less than 30 mL/min) renal impairment have not been studied [see Clinical Pharmacology (12.3)].

8.7 Hepatic Impairment

No dose adjustment is required for patients with mild (bilirubin less than or equal to ULN and AST greater than ULN or bilirubin less than or equal to 1.5 x ULN) or moderate (bilirubin 1.5 to 3 x ULN) hepatic impairment. The effects of severe hepatic impairment (bilirubin greater than 3 x ULN) have not been studied [see Clinical Pharmacology (12.3)].

11 DESCRIPTION

KOMZIFTI contains ziftomenib, a menin inhibitor.

The chemical name is (S)-4-methyl-5-((4-((2-(methylamino)-6-(2,2,2-trifluoroethyl)thieno[2,3-d]pyrimidin-4-yl)amino)piperidin-1-yl)methyl)-1-(2-(4-(methylsulfonyl)piperazin-1-yl)propyl)-1H-indole-2-carbonitrile.

The chemical structure is:

The molecular formula is C33H42F3N9O2S2 and the molecular weight is 717.88 g/mol.

Ziftomenib is a white to off-white powder and is highly soluble in aqueous solution at pH 1.2 and practically insoluble at pH ≥4.

KOMZIFTI (ziftomenib) is available as a 200 mg capsule for oral administration.

Each KOMZIFTI capsule contains 200 mg ziftomenib and the following inactive ingredients: croscarmellose sodium, magnesium stearate, mannitol, microcrystalline cellulose, and sodium lauryl sulfate. The capsule shells, imprinted with black ink, contain the following inactive ingredients: hypromellose and titanium dioxide.

12 CLINICAL PHARMACOLOGY

12.1 Mechanism of Action

Ziftomenib is a menin inhibitor that blocks the interaction of menin and lysine [K]-specific methyltransferase 2A (KMT2A).

Acute leukemias can be driven by mutations in NPM1 that recruit the wild-type menin-KMT2A complex to promoters of leukemogenic genes. Susceptible NPM1 mutations are defined as those that result in loss of the nucleolar localization signal and the insertion of a new nuclear export signal leading to cytoplasmic accumulation of mutant NPM1 protein that disrupts normal cell function and drives leukemogenesis through altered gene expression.

Pharmacologic disruption of the menin-KMT2A protein-protein interaction by ziftomenib blocks oncogenic activity of mutant NPM1, which induces differentiation of leukemic cells as evidenced by increased expression of differentiation markers. In nonclinical studies, ziftomenib demonstrated in vitro and in vivo antitumor activity in models of NPM1-mutant leukemia.

12.2 Pharmacodynamics

Ziftomenib exposure-response relationships have not been fully characterized and the time course of pharmacodynamic response is unknown.

Cardiac Electrophysiology

The effect of KOMZIFTI on the QTc interval was evaluated at 600 mg (the approved recommended dosage) in patients with relapsed or refractory acute myeloid leukemia in KO-MEN-001 (n=133).

The increase in the QTc interval was concentration-dependent with the largest mean increase in QTc interval predicted to be 7.7 ms (upper confidence interval = 12.6 ms) after administration of ziftomenib 600 mg once daily. There were 9 subjects (7%) with QTcF > 500 ms and an increase in QTc > 60 ms over baseline [see Warnings and Precautions (5.2)].

12.3 Pharmacokinetics

Ziftomenib pharmacokinetics were characterized in patients with relapsed or refractory AML. Pharmacokinetic parameters are presented as mean (% CV), unless otherwise specified.

Table 5 Ziftomenib Pharmacokinetics in Patients with R/R AML
Parameter | Dosage
Parameter | 600 mg once daily (with strong CYP3A4 inhibitors) | 600 mg once daily (without CYP3A4 inhibitors)
General Information
Exposurea
Cmax (ng/mL) | 617 (33) | 288 (41)
AUC (ng•h/mL) | 13,185 (36) | 5,512 (48)
Dose Proportionality | Dose proportional over 200 mg to 600 mg once daily doses (0.33 to 1.0 times the recommended dose of 600 mg once daily)
Accumulation | ~ 3-fold
Absorption
Tmax [Median (range)] (hours) | 4.1 (0.5, 8.15)
Absolute Bioavailability | 12.9%
Effect of Food
High-Fat Mealb | AUC and Cmax increased 4-fold
Distribution
Apparent Volume of Distribution (L) | 30100 (98%)
Protein Binding | 99% (albumin)
Elimination
Half-Life (hours) | 189.8 (23) | 93.6 (21)
Apparent Clearance (L/h) | 41.5 (29) | 101.2 (27)
Metabolism
Primary Pathway | CYP3A
Excretion
Feces | 86% (73% as unchanged drug)
Urine | 0.5% (0.03% as unchanged drug)
Abbreviations: Cmax = maximum plasma concentration; AUC = area under the time concentration curve; Tmax = time to peak concentration
a Steady-state (Cycle 2 Day 1).
b Approximately 1,000 calories, 60% fat, 25% carbohydrates, 15% protein.

Specific Populations

No clinically significant differences in the pharmacokinetics of ziftomenib were observed based on age (18 to 86 years), sex, race, ethnicity, mild (bilirubin less than or equal to ULN and AST greater than ULN or bilirubin less than or equal to 1.5 x ULN) or moderate (bilirubin 1.5 to 3 x ULN) hepatic impairment, or mild to moderate (CLCr 30 to 89 mL/min) renal impairment.

The effects of severe hepatic impairment (bilirubin greater than 3 x ULN) or severe renal impairment (CLCr less than 30 mL/min) on ziftomenib pharmacokinetics have not been studied.

Drug Interaction Studies

Clinical Studies and Model-Informed Approaches

Gastric Acid Reducing Agents: Administration of PPIs reduced ziftomenib AUC0-inf by 53% and Cmax by 70%.

Strong, Moderate, or Weak CYP3A4 Inhibitors: Itraconazole, voriconazole, and posaconazole (strong CYP3A4 inhibitors) are estimated to increase ziftomenib AUC by up to 3-fold and Cmax by up to 2-fold.

Erythromycin, fluconazole, and isavuconazole (moderate CYP3A4 inhibitors) are estimated to increase ziftomenib AUC by up to 2-fold and Cmax by up to 2-fold.

Cimetidine (weak CYP3A inhibitor) is estimated to increase ziftomenib AUC and Cmax by up to 1.4-fold.

Strong, Moderate, or Weak CYP3A4 Inducers: Rifampin (strong CYP3A4 inducer) is estimated to decrease ziftomenib AUC by up to 80% and Cmax by up to 70%.

Efavirenz (moderate CYP3A4 inducer) is estimated to decrease ziftomenib AUC and Cmax by up to 70%.

Dexamethasone (weak CYP3A4 inducer) is estimated to decrease ziftomenib AUC and Cmax by up to 40%.

CYP3A4 Substrates: Ziftomenib is predicted to increase the AUC and Cmax of midazolam (CYP3A4 substrate) up to 1.9- and 1.4-fold, respectively, when ziftomenib is administered alone.

Other Drugs: Ziftomenib is not predicted to have clinically significant effects on the exposure of repaglinide (CYP2C8 substrate), (S)-warfarin (CYP2C9 substrate), omeprazole (CYP2C19 substrate), and raltegravir (UGT1A1 substrate).

In Vitro Studies

Cytochrome P450 (CYP450) Enzymes: Ziftomenib does not inhibit CYP1A2 or CYP2D6. Ziftomenib induces CYP1A2 but not CYP2B6 or CYP3A4.

UDP-Glucuronosyltransferase (UGT): Ziftomenib inhibits UGT1A9 and UGT2B17.

Transporter Systems: Ziftomenib is a substrate of P-gp and BCRP, but not BSEP or MRP. Ziftomenib does not inhibit P-gp, BCRP, OAT1, OAT3, OCT2, MATE1, MATE2-K, OATP1B1, OATP1B3, BSEP, or MRP2.

13 NONCLINICAL TOXICOLOGY

13.1 Carcinogenesis, Mutagenesis, Impairment of Fertility

Carcinogenicity studies have not been conducted with ziftomenib. In a repeat dose toxicity study in mice treated with ziftomenib for 13 weeks, lymphoma was observed in multiple organs in one animal.

Ziftomenib was not mutagenic in an in vitro bacterial reverse mutation assay and was not genotoxic in an in vitro micronucleus assay or in an in vivo mouse bone marrow micronucleus assay.

Fertility studies in animals have not been conducted with ziftomenib. In a repeat dose, 13-week toxicity study in dogs treated with twice daily oral administration of ziftomenib at 6, 20, or 60 mg/kg/day, changes were reported in male and female reproductive organs, including decreased mean testis weight, increased vacuolation of the seminiferous tubular epithelial cells, marked decrease in sperm in the epididymal lumen at ≥ 20 mg/kg/day, and fewer developing follicles in the ovaries at ≥ 60 mg/kg/day. At the dose of 20 mg/kg/day in dogs, exposures (AUC) were as low as 0.3 times the human exposure (AUC) at the recommended dose. At the dose of 60 mg/kg/day, exposures were as low as 1.2 times the human exposure at the recommended dose. Reversibility was not assessed at 20 mg/kg/day and findings were not reversible at 60 mg/kg/day after the 4-week recovery period.

13.2 Animal Toxicology and/or Pharmacology

In 13-week repeat-dose toxicity studies in mice and dogs, incidences of hyperplasia in a variety of organs occurred in several animals from both species. The findings in the mouse study were observed at ≥ 12 mg/kg/day at exposures as low as 0.3 times the AUC at the recommended dose, and the findings in the dog study were observed at ≥ 6 mg/kg/day at exposures as low as 0.05 times the AUC at the recommended dose.

14 CLINICAL STUDIES

The efficacy of KOMZIFTI was evaluated in an open-label, single-arm, multicenter clinical trial (Study KO-MEN-001, NCT04067336; KOMET-001) in 112 adult patients with relapsed or refractory AML with an NPM1 mutation identified using next-generation sequencing or polymerase chain reaction. Patients with NPM1 mutations, including Type A, B, and D mutations and other NPM1 mutations likely to result in cytoplasmic localization of the NPM1 protein, were enrolled. Other eligibility criteria included creatinine clearance ≥ 30 mL/min, total bilirubin ≤ 1.5 x the upper limit of normal (ULN), aminotransferases ≤ 2 x ULN, QTcF ≤ 480 msec, and Eastern Cooperative Oncology Group performance status score of 0-2. KOMZIFTI was given orally at a dose of 600 mg once daily until disease progression or unacceptable toxicity. Patients were permitted to resume treatment with KOMZIFTI following hematopoietic stem cell transplant (HSCT). Four (3.6%) of the 112 patients underwent stem cell transplantation following KOMZIFTI treatment.

The baseline demographic and disease characteristics for the 112 treated patients are shown in Table 6.

Table 6 Baseline Demographic and Disease Characteristics in Patients with Relapsed or Refractory AML (Study KO-MEN-001)
Demographics and Disease Characteristics | KOMZIFTI (600 mg once daily) N=112
Demographics
Median Age (years) (Range) | 69 (22, 86)
Age Categories, n (%)
<65 years | 42 (38)
≥65 years | 70 (63)
Sex, n (%)
Male | 49 (44)
Female | 63 (56)
Race, n (%)
White | 88 (79)
Black or African American | 2 (2)
Asian | 4 (4)
Other | 2 (2)
Unknown | 16 (14)
Ethnicity, n (%)
Hispanic or Latino | 3 (3)
Not Hispanic or Latino | 87 (78)
Unknown | 22 (20)
Disease Characteristics
Type of AML, n (%)
De novo AML | 95 (85)
Secondary AML | 17 (15)
Disease status, n (%)
Primary Refractory | 7 (6)
Refractory Relapse | 37 (33)
Untreated Relapse | 68 (61)
Median number of prior lines of therapy (range) | 2 (1, 7)
Prior stem cell transplantation, n (%) | 26 (23)

Efficacy was established based on the rate of complete remission (CR) plus CR with partial hematological recovery (CRh), the duration of CR+CRh, and the rate of conversion from transfusion dependence to transfusion independence. The median follow-up was 4.2 months (range, 0.1 to 41.2 months).

The efficacy results are shown in Table 7.

Table 7 Efficacy Results in Patients with Relapsed or Refractory AML
Endpoint | KOMZIFTI (600 mg once daily) N=112
CRa+CRhb, n (%) | 24 (21.4)
95% CI | (14.2, 30.2)
Median DOCR+CRhc (months) | 5.0
95% CI | (1.9, 8.1)
CRa, n (%) | 19 (17.0)
95% CI | (10.5, 25.2)
Median DOCRd (months) | 5.0
95% CI | (2.8, 8.1)
CRhb, n (%) | 5 (4.5)
95% CI | (1.5, 10.1)
Observed DOCRhe (months) | 0.0^+, 1.5^+, 1.5, 1.6, 11.4
CI: confidence interval; the 95% CI rate was calculated using the exact method based on binomial distribution; NE: not estimable; +: censor.
a CR is defined as bone marrow blasts <5%, absolute neutrophil count (ANC) > 1.0 x 10^9/L, and platelet count > 100 x 10^9/L.
b CRh is defined as bone marrow blasts <5%, (ANC) > 0.5 x 10⁹/L; platelet count > 50 x 10^9/L.
c Duration of CR+CRh (DOCR + CRh) is defined as the time from first CR/CRh to the first documented relapse or death, whichever occurs first.
d Duration of CR (DOCR) is defined as the time from first CR to the first documented relapse or death, whichever occurs first.
e Duration of CRh (DOCRh) is defined as the time from first CRh to the first documented relapse or death, whichever occurs first.

For patients who achieved a CR or CRh, the median time to first response was 2.7 months (range, 0.9 to 15 months). Of the 24 patients who achieved a response of CR or CRh, 21 (88%) patients did so within 6 months of initiating KOMZIFTI.

Among the 66 patients who were dependent on red blood cell (RBC) and/or platelet transfusions at baseline, 14 (21.2%) became independent of RBC and platelet transfusions during any 56-day post-baseline period. Of the 46 patients who were independent of both RBC and platelet transfusions at baseline, 12 (26.1%) patients remained transfusion independent during any 56-day post-baseline period.

16 HOW SUPPLIED/STORAGE AND HANDLING

How Supplied

KOMZIFTI 200 mg capsules are supplied as white capsules printed with “ZIF 200” in black ink.

KOMZIFTI capsules are available in white, induction-sealed, square, high-density polyethylene bottles of 90 capsules with child-resistant closure (NDC 84696-200-90).

Storage

Store at 20°C to 25°C (68°F to 77°F); excursions permitted between 15°C and 30°C (59°F and 86°F) [see USP Controlled Room Temperature].

17 PATIENT COUNSELING INFORMATION

Advise the patient to read the FDA-approved patient labeling (Medication Guide).

Differentiation Syndrome

Advise patients of the risk of developing differentiation syndrome as early as 3 days after the start of therapy and during treatment. Instruct patients to immediately report any symptoms suggestive of differentiation syndrome, such as fever, joint or bone pain, dizziness, shortness of breath or difficulty breathing, cough, chest pain, rapid weight gain, rash, decreased urinary output, or swelling in the hands, feet, ankles, or legs, to their healthcare provider for further evaluation [see Boxed Warning and Warnings and Precautions (5.1)].

Prolonged QT Interval

Advise patients to consult their healthcare provider immediately if they feel faint, lose consciousness, or have signs or symptoms suggestive of arrhythmia. Advise patients with a history of hypokalemia or hypomagnesemia of the importance of monitoring their electrolytes [see Warnings and Precautions (5.2)].

Embryo-Fetal Toxicity

Advise pregnant women and females of reproductive potential of the potential risk to a fetus. Advise females of reproductive potential to notify their healthcare provider of a known or suspected pregnancy [see Warnings and Precautions (5.3), Use in Specific Populations (8.1)].

Advise females of reproductive potential to use effective contraception during treatment with KOMZIFTI and for 6 months after the last dose. Advise males with female partners of reproductive potential to use effective contraception during treatment with KOMZIFTI and for 3 months after the last dose [see Use in Specific Populations (8.3)].

Lactation

Advise women not to breastfeed during treatment with KOMZIFTI and for 2 weeks after the last dose [see Use in Specific Populations (8.2)].

Drug Interactions

Advise patients to inform their healthcare providers of all concomitant medications, including over-the-counter medications and supplements [see Drug Interactions (7.1)].

Dosing Instructions

- Advise patients to take KOMZIFTI once daily, at around the same time each day, on an empty stomach, at least 1 hour before or 2 hours after a meal [see Dosage and Administration (2.3)].
- Advise patients to swallow KOMZIFTI capsules whole. Do not open, break, or chew the capsules [see Dosage and Administration (2.3)].
- Instruct patients, if they miss a dose of KOMZIFTI, to take the dose as soon as possible on the same day and at least 12 hours prior to the next scheduled dose and return to the normal schedule the following day. Advise patients not to take 2 doses within 12 hours to make up for the missed dose [see Dosage and Administration (2.3)].

Manufactured for
Kura Oncology, Inc., San Diego, CA 92121
KOMZIFTI™ is a trademark of Kura Oncology, Inc.
© 2025 Kura Oncology, Inc.

MEDICATION GUIDE
KOMZIFTI (kom-ZIF-tee)
(ziftomenib) capsules

What is the most important information I should know about KOMZIFTI?
KOMZIFTI can cause serious side effects including:
Differentiation Syndrome. Differentiation syndrome is a condition that affects your blood cells that is common during treatment with KOMZIFTI and can be life-threatening or lead to death if not treated. Differentiation syndrome can happen as early as 3 days after you start KOMZIFTI treatment and can also happen later during treatment with KOMZIFTI. Tell your healthcare provider or go to the nearest hospital emergency room right away if you develop any of the following signs or symptoms of differentiation syndrome during treatment with KOMZIFTI:

- fever
- joint or bone pain
- dizziness
- shortness of breath or trouble breathing
- cough

- chest pain
- rapid weight gain
- rash
- decreased urine output
- swelling of hands, feet, ankles, or legs

If you develop signs and symptoms of differentiation syndrome during treatment with KOMZIFTI, your healthcare provider may temporarily stop KOMZIFTI and give you a corticosteroid medicine. Your healthcare provider will monitor you until your signs and symptoms improve.
See “What are the possible side effects of KOMZIFTI?” for more information about side effects.

What is KOMZIFTI?
KOMZIFTI is a prescription medicine used to treat adults with acute myeloid leukemia (AML) with a nucleophosmin 1 (NPM1) mutation whose AML has come back or did not improve after previous treatment(s) and who have no other satisfactory treatment options.
Your healthcare provider will perform a test to make sure that KOMZIFTI is right for you.
It is not known if KOMZIFTI is safe and effective in children.

Before taking KOMZIFTI, tell your healthcare provider about all of your medical conditions, including if you:

- have any heart problems, including a condition called long QT syndrome.
- have problems with abnormal levels of salts in your blood (electrolytes), such as potassium and magnesium levels.
- are pregnant or plan to become pregnant. KOMZIFTI can harm your unborn baby.
  Females who are able to become pregnant:
  - Your healthcare provider will perform a pregnancy test before you start treatment with KOMZIFTI.
  - Use effective birth control (contraception) during treatment with KOMZIFTI and for 6 months after the last dose.
  Males who have female partners who are able to become pregnant:
  - Use effective birth control (contraception) during treatment with KOMZIFTI and for 3 months after the last dose.
  - Talk to your healthcare provider about birth control methods you can use during this time.
- are breastfeeding or plan to breastfeed. It is not known if KOMZIFTI passes into your breast milk. Do not breastfeed during your treatment with KOMZIFTI and for 2 weeks after your last dose.

Tell your healthcare provider about any other medicines you take, including prescription and over-the-counter medicines, vitamins, and herbal supplements.
KOMZIFTI and other medicines may affect each other causing side effects. Know the medicines you take. Keep a list of them to show your healthcare provider and pharmacist.

How should I take KOMZIFTI?

- Take KOMZIFTI exactly as your healthcare provider tells you to.
- Do not change your dose or stop taking KOMZIFTI without talking to your healthcare provider.
- Take KOMZIFTI 1 time a day around the same time each day.
- Take KOMZIFTI on empty stomach, at least 1 hour before or 2 hours after a meal.
- Swallow KOMZIFTI capsules whole. Do not open, break, or chew the capsules.
- If you take medicine to reduce stomach acid:
  - Avoid taking a proton pump inhibitor (PPI) medicine with KOMZIFTI.
  - Take KOMZIFTI either 2 hours before or 10 hours after taking an H2 receptor blocker medicine.
  - Take KOMZIFTI either 2 hours before or 2 hours after taking a locally acting antacid medicine (such as calcium carbonate).
- If you miss a dose of KOMZIFTI or did not take it at the usual time, take your dose as soon as possible and at least 12 hours before your next scheduled dose. Return to your normal schedule the following day. Do not take 2 doses within 12 hours of each other to make up for the missed dose.

What are the possible side effects of KOMZIFTI?
KOMZIFTI can cause serious side effects, including:

- See “What is the most important information I should know about KOMZIFTI?”
- Changes in electrical activity of your heart (QT prolongation). Changes in the electrical activity of your heart may lead to irregular heartbeats (rhythm) that can be life-threatening or lead to death. Your healthcare provider will check the electrical activity of your heart with a test called an electrocardiogram (ECG) and will also do blood tests to check your potassium and magnesium levels before and during treatment with KOMZIFTI. Tell your healthcare provider right away if you feel faint, lightheaded, or dizzy, or if you have shortness of breath, or if you feel your heart beating irregularly or fast during treatment with KOMZIFTI.

The most common side effects of KOMZIFTI include:

- infections including bacterial infections
- bleeding
- diarrhea
- nausea
- feeling tired

- swelling in the arms and legs
- muscle, bone, and joint pain
- itching
- fever with decreased white blood cell counts
- changes in liver function tests

Your healthcare provider may decrease your dose, temporarily stop, or completely stop your treatment with KOMZIFTI if you develop certain side effects during treatment with KOMZIFTI.
KOMZIFTI may cause fertility problems in females and males, which may affect your ability to have children. Talk to your healthcare provider if this is a concern for you.
These are not all of the possible side effects of KOMZIFTI.
Call your doctor for medical advice about side effects. You may report side effects to FDA at 1-800-FDA-1088.

How should I store KOMZIFTI?

- Store KOMZIFTI at room temperature between 68°F to 77°F (20°C to 25°C).
- KOMZIFTI comes in a container with a child-resistant cap.

Keep KOMZIFTI and all medicines out of the reach of children.

General information about the safe and effective use of KOMZIFTI.
Medicines are sometimes prescribed for purposes other than those listed in a Medication Guide. Do not take KOMZIFTI for conditions for which it was not prescribed. Do not give KOMZIFTI to other people, even if they have the same symptoms you have. It may harm them. You can ask your pharmacist or healthcare provider for information about KOMZIFTI that is written for health professionals.

What are the ingredients in KOMZIFTI?
Active ingredient: ziftomenib
Inactive ingredients: croscarmellose sodium, magnesium stearate, mannitol, microcrystalline cellulose, and sodium lauryl sulfate.
The capsule shells imprinted with black ink contain: hypromellose and titanium dioxide.
Manufactured for: Kura Oncology, Inc., San Diego, CA 92121
KOMZIFTITM is a trademark of Kura Oncology, Inc.
Copyright © 2025 Kura Oncology, Inc.
For more information, go to www.komzifti.com or call Kura at 1-844-587-2662

This Medication Guide has been approved by the U.S. Food and Drug Administration.

Issued: 11/2025

Principal Display Panel - 200 mg Bottle Label

NDC 84696-200-90

komzifti™
(ziftomenib)
capsules

200 mg

Dispense the enclosed
Medication Guide to
each patient.

Rx Only

90 capsules

KURA®
ONCOLOGY

KYOWA KIRIN